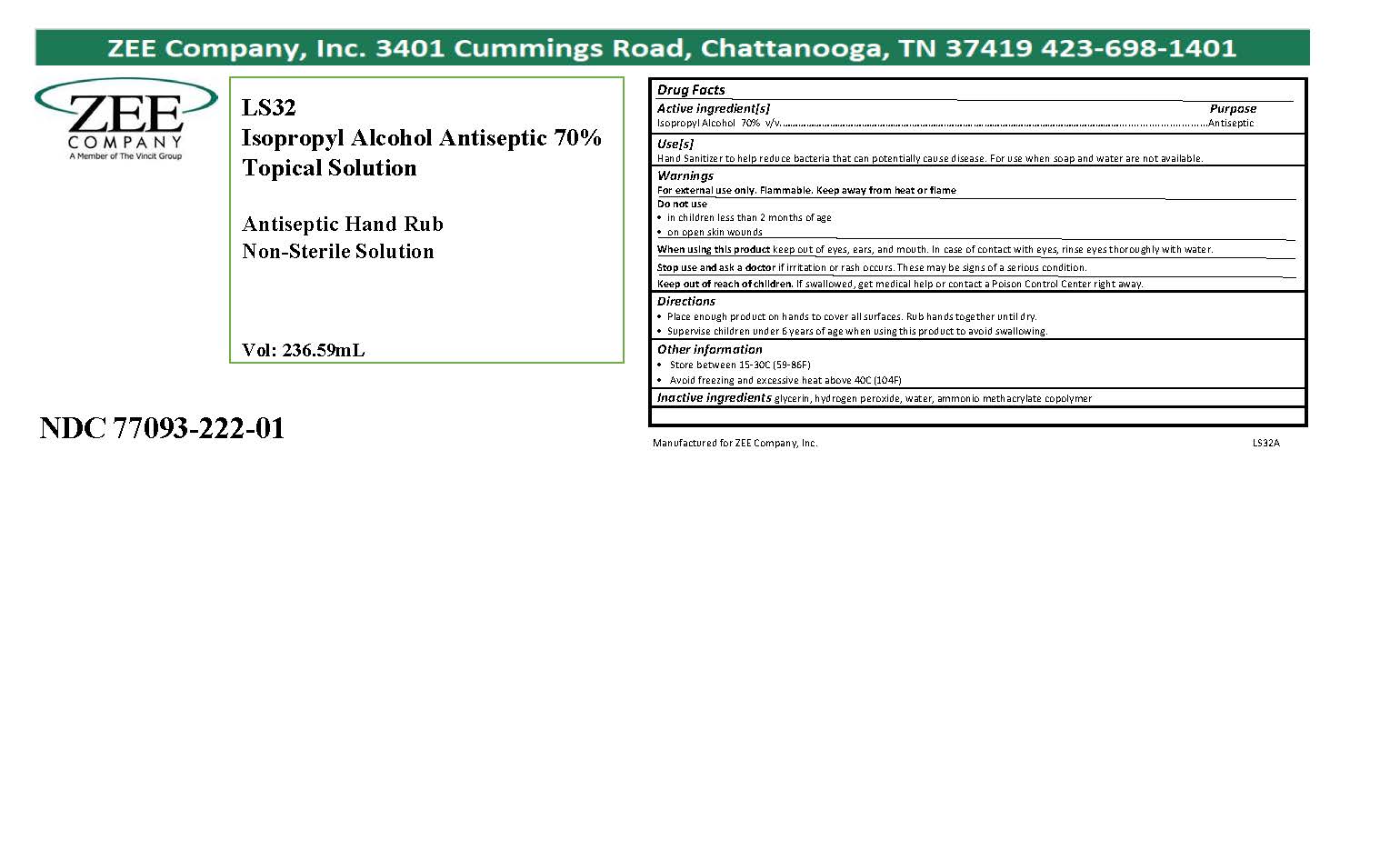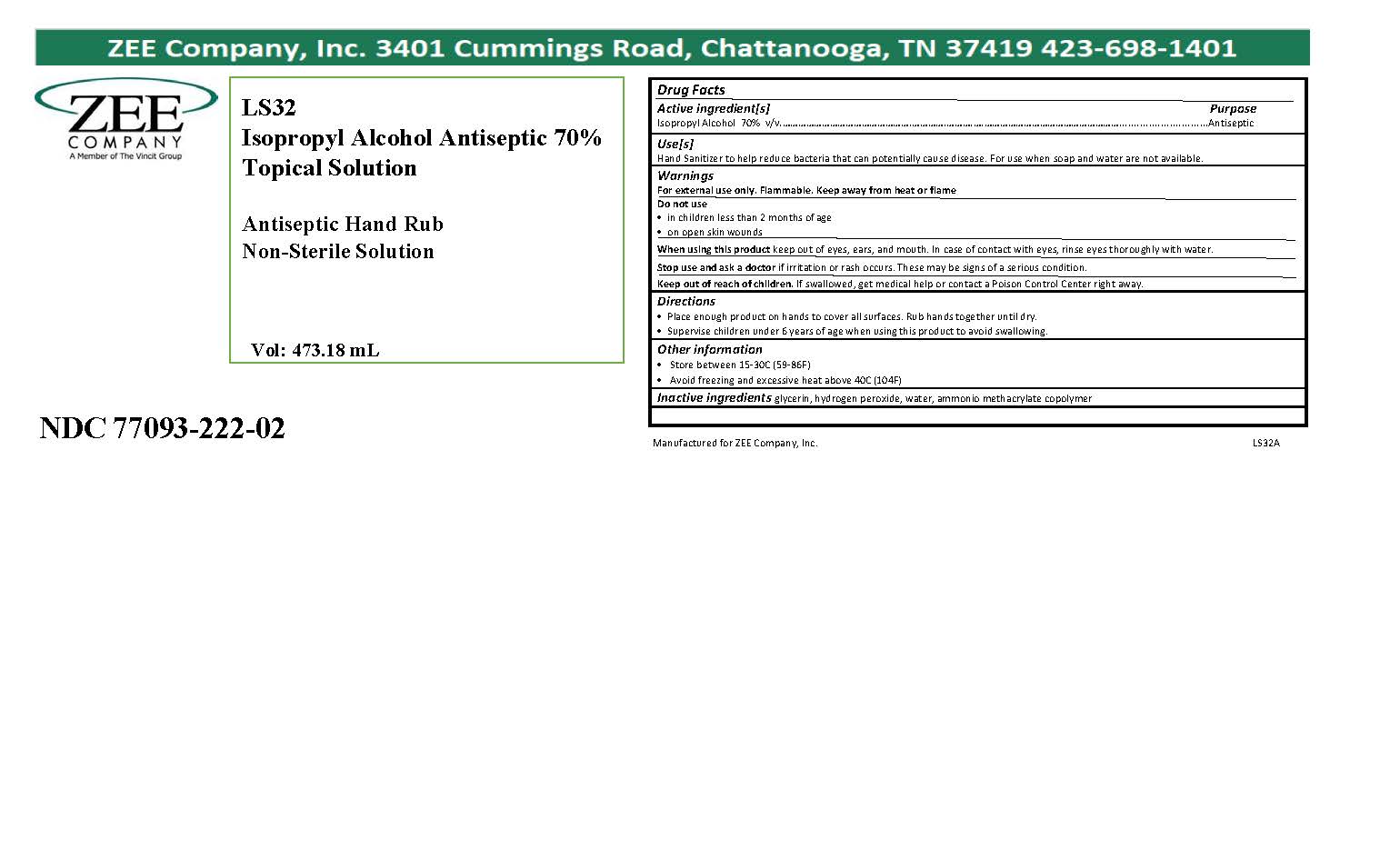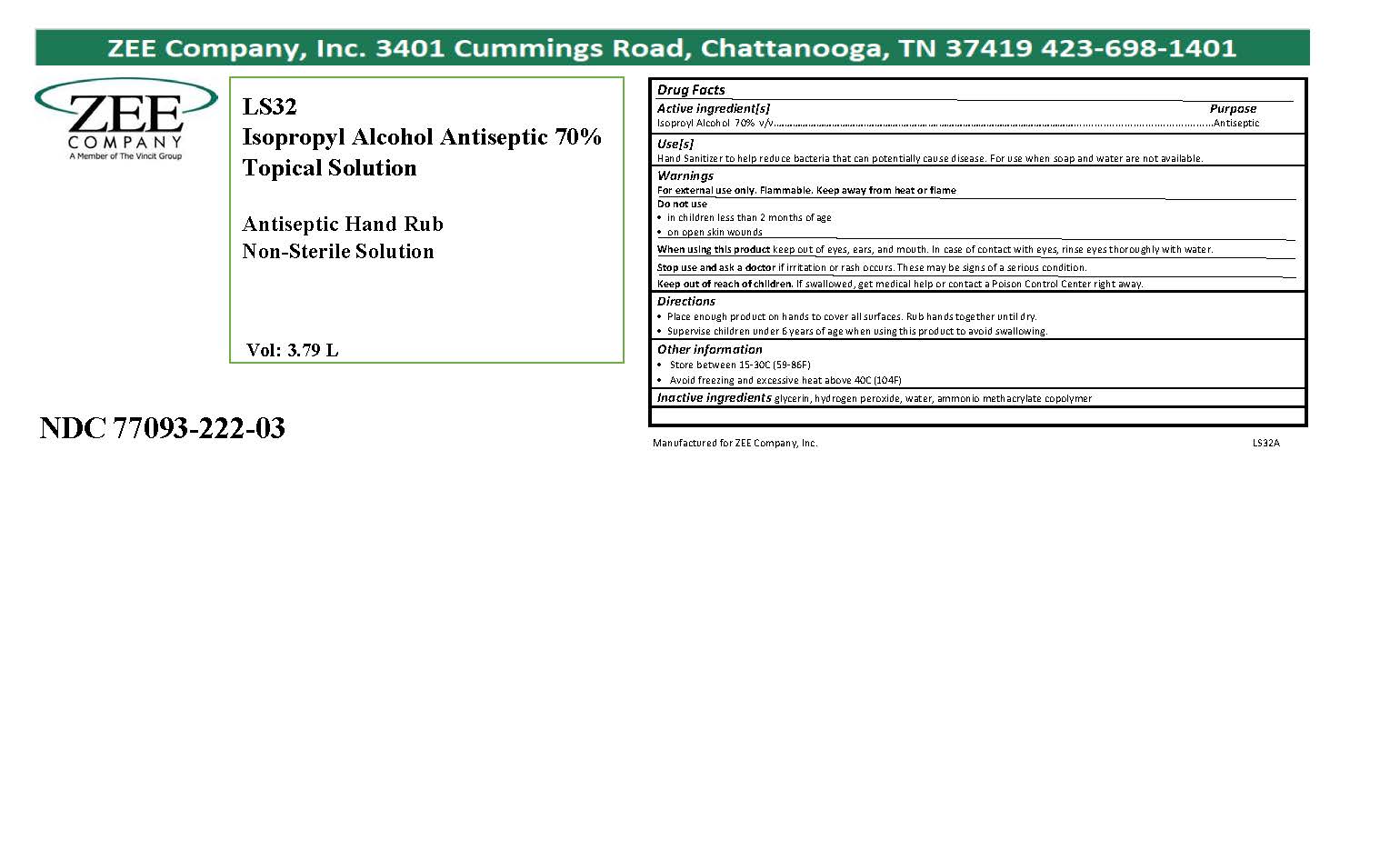 DRUG LABEL: LS32
NDC: 77093-222 | Form: LIQUID
Manufacturer: Vincit Zee Company
Category: otc | Type: HUMAN OTC DRUG LABEL
Date: 20200520

ACTIVE INGREDIENTS: ISOPROPYL ALCOHOL 70 mL/100 mL
INACTIVE INGREDIENTS: AMMONIUM POLYACRYLOYLDIMETHYL TAURATE (55000 MPA.S); HYDROGEN PEROXIDE; GLYCERIN; WATER

LS32 Cummings Rd.

active ingredient

Isopropyl Alcohol

purpose

Antiseptic

INDICATIONS AND USAGE

Keep out of eyes, ears, and mouth. In case of contact with eyes, rinse eyes thoroughly with water.

WARNINGS

For external use only. Flammable. Keep away from heat and open flame.

Do not use on children less than 2 months of age or on open skin wounds.

WHEN USING

Keep out of eyes, ears, and mouth. In case of contact with eyes, rinse eyes thoroughly with water.

Stop use and ask a doctor if irritation or rash occurs. These may be signs of a serious condition.

Keep out of reach of children. If swallowed get medical help or contact a Poison Control Center right away.

DOSAGE AND ADMINISTRATION

Place enough product on hands to cover all surfaces. Rub hands together until dry.

Supervise children under 6 years of age when using this product to avoid swallowing.

other safety information

Store between 15-30C (59-86F). Avoid freezing and excessive heat above 40C (104F)

INACTIVE INGREDIENT

Glycerin, Water, Hydrogen Peroxide, Ammonium Polyacryloyldimethyl Taurate

LS32 Product Labels

236.59ml NDC Code: 77093-222-01

473.18ml NDC Code: 77093-222-02

3785ml NDC Code: 77093-222-03